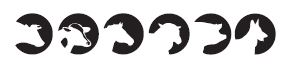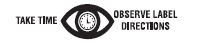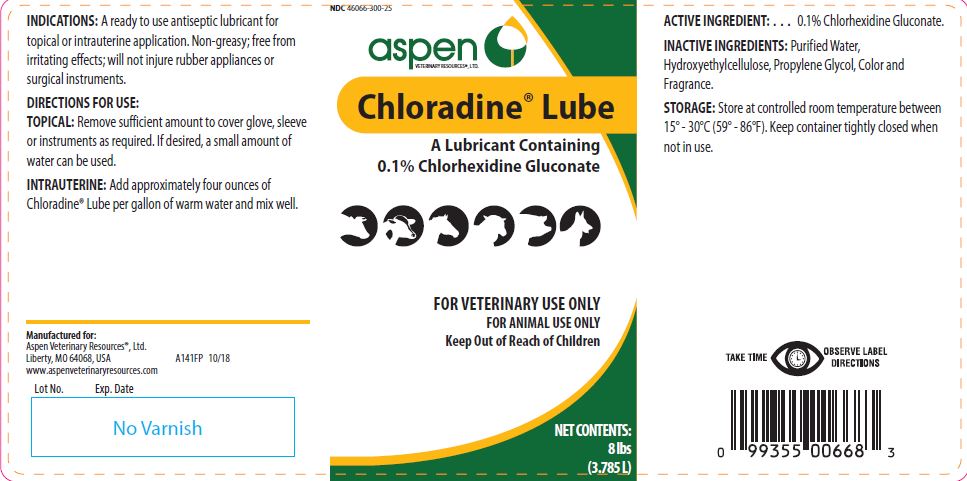 DRUG LABEL: Chloradine Lube
NDC: 46066-300 | Form: JELLY
Manufacturer: ASPEN VETERINARY
Category: animal | Type: OTC ANIMAL DRUG LABEL
Date: 20251016

ACTIVE INGREDIENTS: CHLORHEXIDINE GLUCONATE 5.56 g/1 L

Chloradine® Lube

PURPOSE

A Lubricant Containing 0.1% Chlorhexidine Gluconate

KEEP OUT OF REACH OF CHILDREN

FOR VETERINARY USE ONLY
FOR ANIMAL USE ONLY
Keep Out of Reach of Children

NET CONTENTS:

8 lbs (3.785 L)

INDICATIONS:

A ready to use antiseptic lubricant for topical or intrauterine application. Non-Greasy; free from irritating effects; will not injure rubber appliances or surgical instruments.

DIRECTIONS FOR USE:

TOPICAL: Remove sufficient amount to cover glove, sleeve or instruments as required. If desired, a small amount of water can be used.
INTRAUTERINE: Add approximately four ounces of Chloradine® Lube per gallon of warm water and mix well.

ACTIVE INGREDIENT:

. . . 0.1% Chlorhexidine Gluconate.

INACTIVE INGREDIENTS:

Purified Water, Hydroxyethylcellulose, Propylene Glycol, Color and Fragrance.

STORAGE:

Store at controlled room temperature between 15° - 30°C (59° - 86°F). Keep container tightly closed when not in use.

INFORMATION FOR OWNERS/CAREGIVERS

Manufactured for:
Aspen Veterinary Resources®, Ltd.
Liberty, MO 64068, USA A141FP 10/18
www.aspenveterinaryresources.com